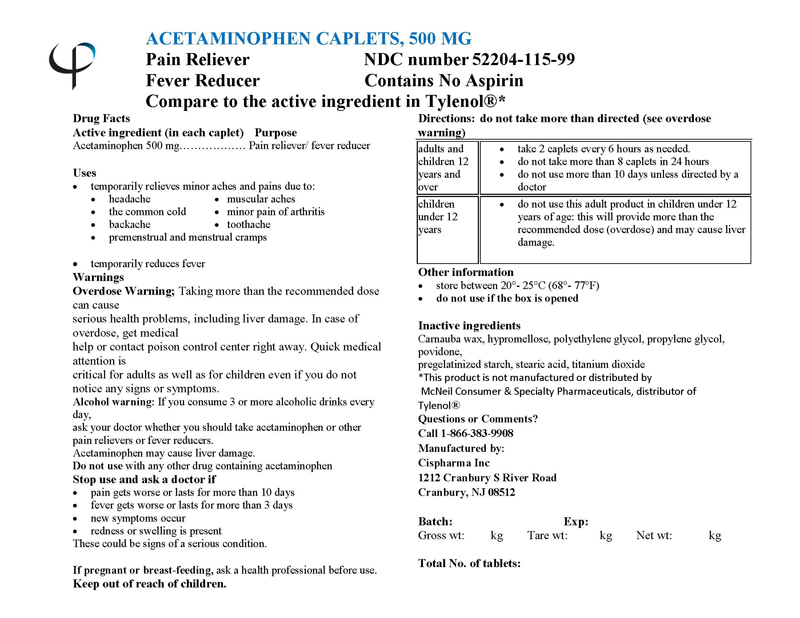 DRUG LABEL: ACETAMINOPHEN
NDC: 52204-115 | Form: TABLET
Manufacturer: Cispharma, Inc
Category: otc | Type: HUMAN OTC DRUG LABEL
Date: 20110405

ACTIVE INGREDIENTS: ACETAMINOPHEN 500 mg/1 1
INACTIVE INGREDIENTS: CARNAUBA WAX; HYPROMELLOSE 2910 (5 MPA.S); POLYETHYLENE GLYCOL; PROPYLENE GLYCOL; POVIDONE; STARCH, PREGELATINIZED CORN; STEARIC ACID; TITANIUM DIOXIDE

ACETAMINOPHEN CAPLETS, 500 mg

Drug Facts

Active ingredient (in each caplet)

Acetaminophen .....................500 mg

PURPOSE

Pain Reliever/ Fever Reducer

Uses

Temporarily relieves minor aches and pains due to:

- headache
- the common cold
- backache
- muscular aches
- minor pain of arthritis
- toothache
- premenstrual and menstrual cramps

temporarily reduces fever

Warnings

Alcohol warning: If you consume 3 or more alcoholic drinks every day, ask your doctor whether you should take acetaminophen or other pain relievers or fever reducers. Acetaminophen may cause liver damage.

Do not use with any other drug containing acetaminophen

Stop use and ask a doctor if

- pain gets worse or lasts for more than 10 days
- fever gets worse or lasts for more than 3 days
- new symptoms occur
- redness or swelling is present

These could be signs of a serious condition.

INDICATIONS AND USAGE

Indicated for pain relief.

PREGNANCY OR BREAST FEEDING

If pregnant or breast-feeding, ask a health professional before use.

Keep out of reach of children.

Overdose Warning:

Taking more than the recommended dose can cause serious health problems, including liver damage. In case of overdose, get medical help or contact poison control center right away. Quick medical attention is critical for adults as well as for children even if you do not notice any signs or symptoms.

Directions: do not take more than directed (see overdose warning)

adults and children 12 years and over | - take 2 caplets every 6 hours as needed. - do not take more than 8 caplets in 24 hours - do not use more than 10 days unless directed by a doctor
children under 12 years | - do not use this adult product in children under 12 years of age: this will provide more than the recommended dose (overdose) and may cause liver damage.

Other Information

- store between 20°- 25°C (68°- 77°F)
- do not use if the box is opened

Inactive Ingredients

Carnauba wax, hypromellose, polyethylene glycol, propylene glycol, povidone, pregelatinized starch, stearic acid, titanium dioxide

This product is not manufactured or distributed by McNeil Consumer & Specialty Pharmaceuticals, distributor of Tylenol®

Questions or Comments?
Call 1-866-383-9908

Manufactured by:

Cispharma Inc
1212 Cranbury S River Road
Cranbury, NJ 08512